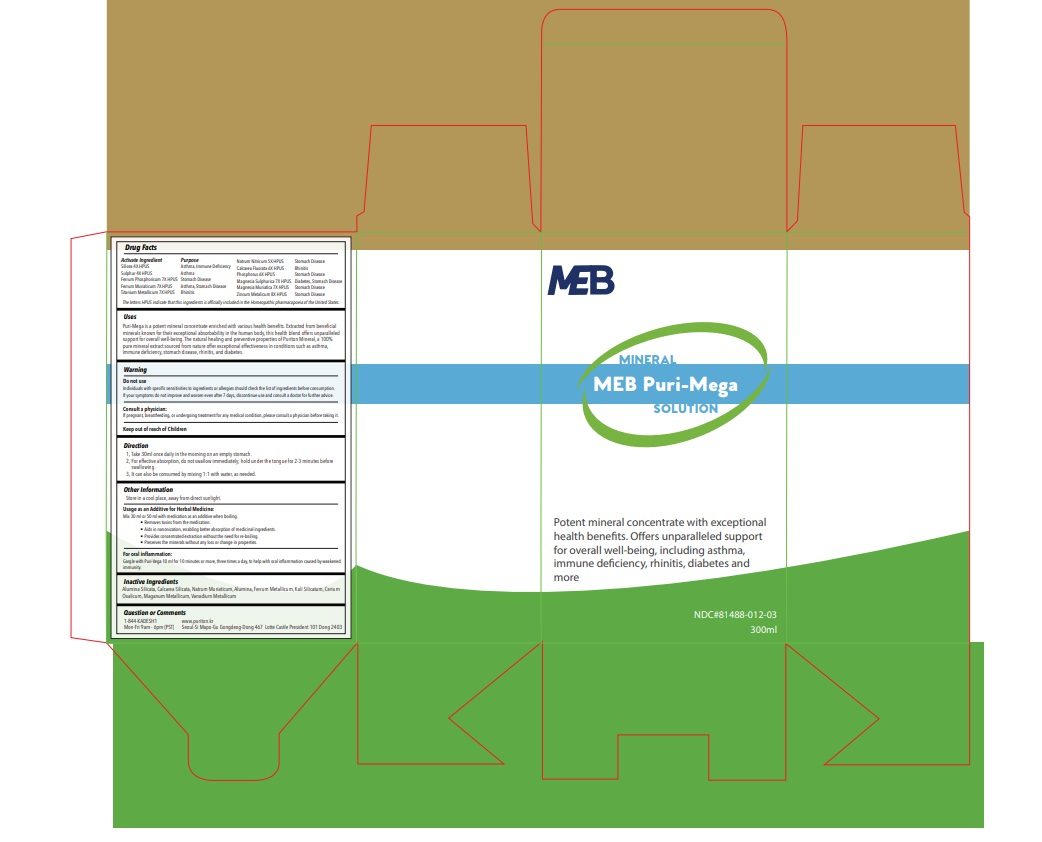 DRUG LABEL: MEB Puri-Mega
NDC: 81488-012 | Form: LIQUID
Manufacturer: Kadesh Incoporation Co,Ltd
Category: homeopathic | Type: HUMAN OTC DRUG LABEL
Date: 20230727

ACTIVE INGREDIENTS: TITANIUM 7 [hp_X]/300 mL; SODIUM NITRATE 5 [hp_X]/300 mL; FERROSOFERRIC PHOSPHATE 7 [hp_X]/300 mL; CALCIUM FLUORIDE 6 [hp_X]/300 mL; MAGNESIUM SULFATE HEPTAHYDRATE 7 [hp_X]/300 mL; SULFUR 4 [hp_X]/300 mL; MAGNESIUM CHLORIDE 7 [hp_X]/300 mL; SILICON DIOXIDE 4 [hp_X]/300 mL; PHOSPHORUS 6 [hp_X]/300 mL; ZINC 8 [hp_X]/300 mL; FERRIC CHLORIDE HEXAHYDRATE 7 [hp_X]/300 mL
INACTIVE INGREDIENTS: KAOLIN; MANGANESE; CEROUS OXALATE NONAHYDRATE; IRON; CALCIUM SILICATE; SODIUM CHLORIDE; ALUMINUM OXIDE; POTASSIUM SILICATE; VANADIUM

ACTIVE INGREDIENT

Silicea, Sulphur, Ferrum Phosphoricum, Ferrum Muriaticum, Titanium Metallicum, Natrum Nitricum, Calcarea Fluorata, Phosphorus, Magnesia Sulphurica, Magnesia Muriatica, Zincum Metalicum

INDICATIONS AND USAGE

MEB Puri-Mega

“Potent mineral concentrate with exceptional health benefits. Offers unparalleled support for overall well-being, including asthma, immune deficiency, rhinitis, diabetes and more.”

Usage:

Puri-Mega is a potent mineral concentrate enriched with various health benefits. Extracted from beneficial minerals known for their exceptional absorbability in the human body, this health blend offers unparalleled support for overall well-being. The natural healing and preventive properties of Puriton Mineral, a 100% pure mineral extract sourced from nature offer exceptional effectiveness in conditions such as asthma, immune deficiency, stomach disease, rhinitis, and diabetes.

Do not Use

Individuals with specific sensitivities to ingredients or allergies should check the list of ingredients before consumption.

If your symptoms do not improve and worsen even after 7 days, discontinue use and consult a doctor for further advice.

Consult a physician:

If pregnant, breastfeeding, or undergoing treatment for any medical condition, please consult a physician before taking it.

DOSAGE AND ADMINISTRATION

Take 30ml once daily in the morning on an empty stomach.

For effective absorption, do not swallow immediately; hold under the tongue for 2-3 minutes before swallowing.

It can also be consumed by mixing 1:1 with water, as needed.

Usage as an Additive for Herbal Medicine:

Mix 30 ml or 50 ml with medication as an additive when boiling.

Removes toxins from the medication.

Aids in nanonization, enabling better absorption of medicinal ingredients.

Provides concentrated extraction without the need for re-boiling.

Preserves the minerals without any loss or change in properties.

For oral inflammation:

Gargle with Puri-Mega 10 ml for 10 minutes or more, three times a day, to help with oral inflammation caused by weakened immunity.

DO NOT USE

Individuals with specific sensitivities to ingredients or allergies should check the list of ingredients before consumption.

If your symptoms do not improve and worsen even after 7 days, discontinue use and consult a doctor for further advice

Active Ingredients Purpose

Silicea 4X HPUS ………………………………….. Asthma, immune deficiency

Sulphur 4X HPUS………………………………….. Asthma

Ferrum Phosphoricum 7X HPUS.………………… Stomach Disease

Ferrum Muriaticum 7X HPUS…………………….. Asthma, Stomach Disease

Titanium Metallicum 7X……………………………. Rhinitis

Natrum Nitricum 5X HPUS……………………….. Stomach Disease

Calcarea Fluorata 6X HPUS……………………… Rhinitis

Phosphorus 6X HPUS…………………………….. Stomach Disease

Magnesia Sulphurica 7X HPUS …………………. Diabetes, Stomach Disease

Magnesia Muriatica 7X HPUS…………………. Stomach Disease

Zincum Metalicum 8X …………………………….. Stomach Disease

ASK DOCTOR

If pregnant, breastfeeding, or undergoing treatment for any medical condition, please consult a physician before taking it.

INACTIVE INGREDIENT

Alumina Silicata, Calcarea Silicata, Natrum Muriaticum, Alumina, Ferrum Metallicum, Kali Silicatum, Cerium Oxalicum, Maganum Metallicum, Vanadium Metallicum

QUESTIONS

1-844-KADESH1

Mon-Fri 9am - 6pm (PST)

www.puriton.kr

Seoul-Si Mapo-Gu Gongdeog-Dong 467

Lotte Castle President 101 Dong 2403

OTHER SAFETY INFORMATION

Store in a cool place, away from direct sunlight

PACKAGE LABEL

MEB Puri-Mega. NDC : 81488-012-03 (300ML)
MEB Puri-Mega. NDC : 81488-012-10 (1000ML)